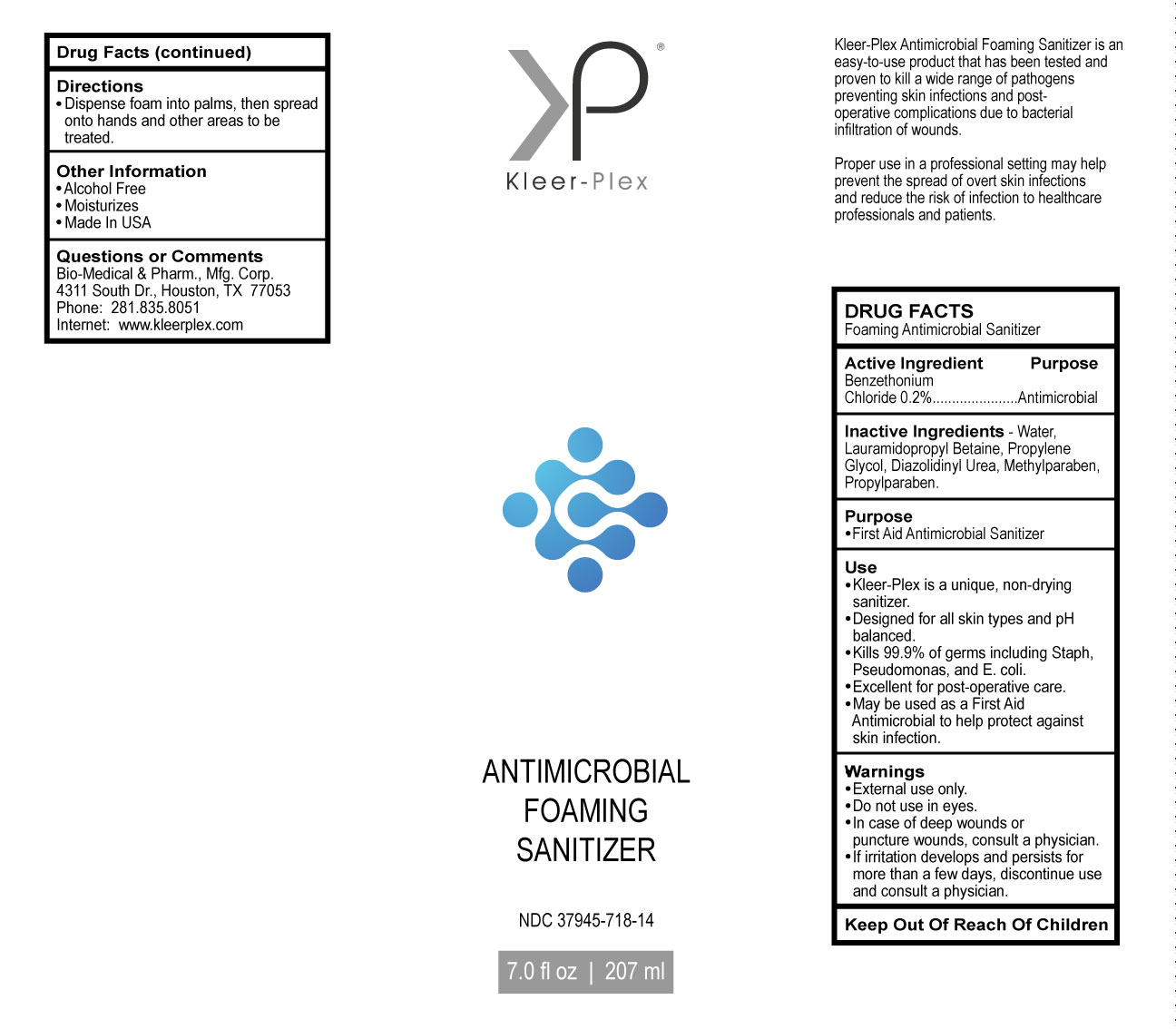 DRUG LABEL: ANTIMICROBIAL FOAMING SANITIZER
NDC: 37945-718 | Form: LIQUID
Manufacturer: Bio-Medical & Pharmaceutical Manufacturing Corporation
Category: otc | Type: HUMAN OTC DRUG LABEL
Date: 20181106

ACTIVE INGREDIENTS: BENZETHONIUM CHLORIDE 0.2 g/100 g
INACTIVE INGREDIENTS: PROPYLPARABEN; LAURAMIDOPROPYL BETAINE; 2-HEXENAL PROPYLENE GLYCOL ACETAL, (1E)-; DIAZOLIDINYL UREA; METHYLPARABEN

DRUG FACTS

Foaming Antimicrobial Sanitizer

Active Ingredient

Benzethonium Chloride 0.2%

PURPOSE

Antimicrobial

Inactive Ingredients

Water,Lauramidopropyl Betaine, Propylene Glycol, Diazolidinyl Urea, Methylparaben,Propylparaben.

Purpose

First Aid Antimicrobial Sanitizer

Use

Kleer-Plex is a unique, non-drying sanitizer. Designed for all skin types and pH balanced. Kills 99.9% of germs including Staph,

Pseudomonas, and E. coli. Excellent for post-operative care. May be used as a First Aid Antimicrobial to help protect against

skin infection.

Warnings

External use only. Do not use in eyes. In case of deep wounds or puncture wounds, consult a physician. If irritation develops and persists for more than a few days, discontinue use and consult a physician. .

Other Information

Alcohol Free

Moisturizes

Made In USA

Questions or Comments

Bio-Medical & Pharm., Mfg. Corp.

4311 South Dr., Houston, TX 77053

Phone: 281.835.8051

Internet: www.kleerplex.com

Directions

Dispense foam into palms, then spread onto hands and other areas to be treated.

PACKAGE LABEL

Kleer-Plex

ANTIMICROBIAL

FOAMING

SANITIZER

7.0 fl oz | 207 ml